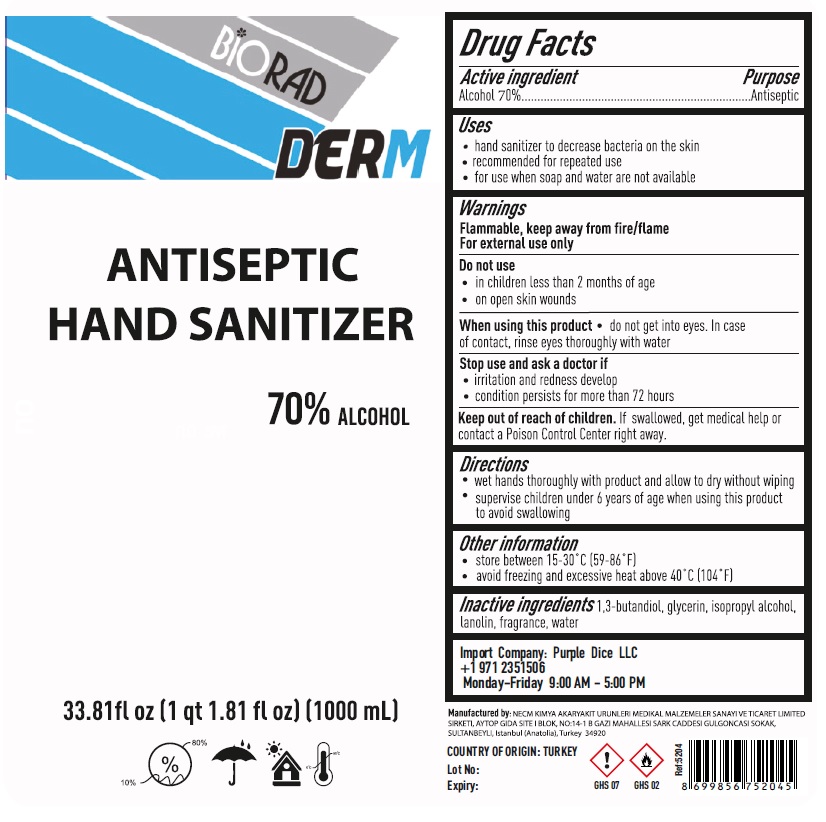 DRUG LABEL: ANTISEPTIC HAND SANITIZER
NDC: 79455-001 | Form: LIQUID
Manufacturer: NECM KIMYA AKARYAKIT URUNLERI MEDIKAL MALZEMELER SANAYI VE TICARET LIMITED SIRKETI
Category: otc | Type: HUMAN OTC DRUG LABEL
Date: 20200710

ACTIVE INGREDIENTS: ALCOHOL 70 L/100 L
INACTIVE INGREDIENTS: BUTYLENE GLYCOL; GLYCERIN; ISOPROPYL ALCOHOL; LANOLIN; WATER

BiORAD DERM ANTISEPTIC HAND SANITIZER

Active ingredient

Alcohol 70%

Purpose

Antiseptic

Uses

- hand sanitizer to decrease bacteria on the skin
- recommended for repeated use
- for use when soap and water are not available

Warnings

Flammable, keep away from fire/flame

For external use only

Do not use
• in children less than 2 months of age
• on open skin wounds

When using this product • do not get into eyes. In case of contact, rinse eyes thoroughly with water

Stop use and ask a doctor if

- irritation and redness develop
- condition persists for more than 72 hours

Keep out of reach of children. If swallowed, get medical help or contact a Poison Control Center right away.

Directions

- wet hands thoroughly with product and allow to dry without wiping
- supervise children under 6 years of age when using this product to avoid swallowing

Other information

- store between 15-30°C (59-86°F)
- avoid freezing and excessive heat above 40°C (104°F)

Inactive ingredients

1,3-butandiol, glycerin, isopropyl alcohol, lanolin, fragrance, water

Import Company: Purple Dice LLC

+1-971-235-1506

Monday-Friday 9:00 AM - 5:00 PM

Manufactured by: NECM KIMYA AKARYAKIT URUNLERI MEDIKAL MALZEMELER SANAYI VE TICARET LIMITED
SIRKETI, AYTOP GIDA SITE I BLOK, NO:14-1 B GAZI MAHALLESI SARK CADDESI GULGONCASI SOKAK,
SULTANBEYLI, Istanbul (Anatolia), Turkey 34920

COUNTRY OF ORIGIN: TURKEY